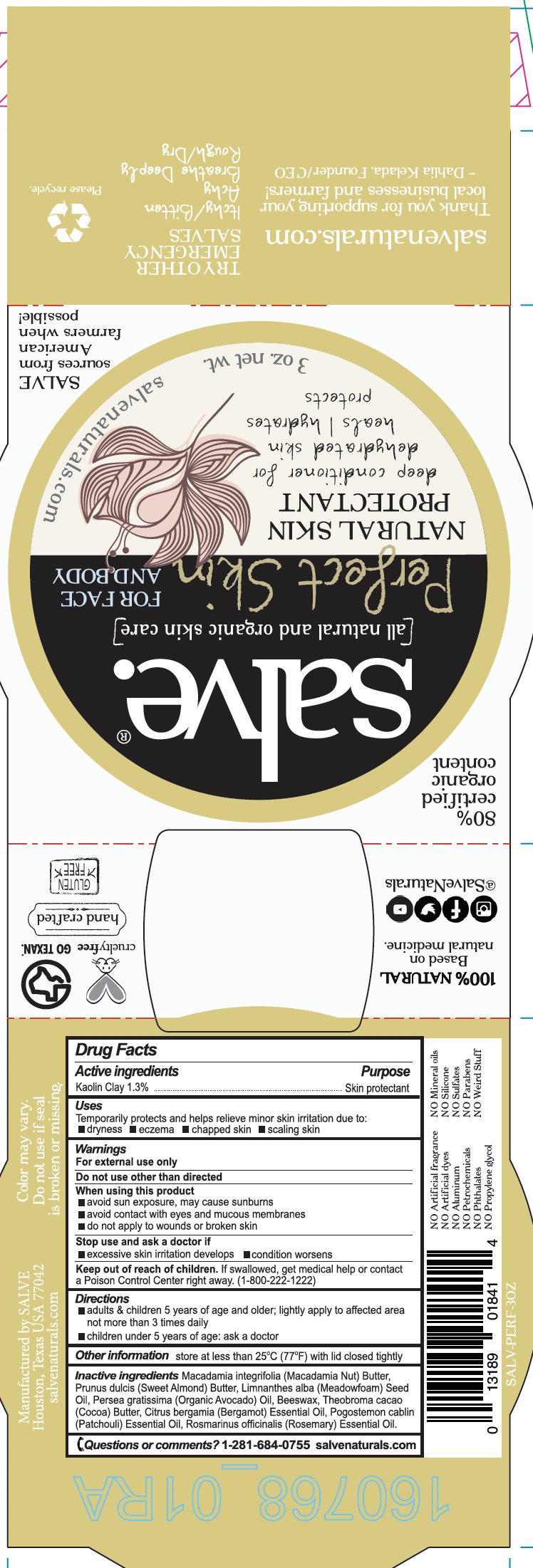 DRUG LABEL: Perfect Skin Face Salve
NDC: 71157-0022 | Form: CREAM
Manufacturer: Kelada Creative Group
Category: otc | Type: HUMAN OTC DRUG LABEL
Date: 20171016

ACTIVE INGREDIENTS: ZINC OXIDE 2.4 g/0.259 mL
INACTIVE INGREDIENTS: SUNFLOWER OIL; TEA TREE OIL; WHITE WAX; CEDRUS DEODARA WOOD OIL; ARGAN OIL; MEADOWFOAM SEED OIL; AVOCADO OIL; CANANGA OIL

Perfect Skin Face Salve

ACTIVE INGREDIENT

Kaolin Clay 1.3%

PURPOSE

Temporarily protects and helps relieve minor skin irritation due to dryness, eczema, chapped skin, and scaling skin.

WARNINGS

For external use only

Do not use other than as directed

When using this product

- avoid sun exposure, may cause sunburns
- avoid contact with eyes and mucous membranes
- do not apply to wounds or broken skin

DOSAGE AND ADMINISTRATION

Temporarily protects and helps relieve minor skin irritation due to dryness, eczema, chapped skin, and scaling skin.

Keep out of reach of children. If swallowed, get medical help or contact a Poison Control Center right away.

INACTIVE INGREDIENT

Macadamia nut butter, Sweet almond butter, Meadowfoam seed oil, Organic avocado oil, Beeswax, Cocoa butter, Bergamot essential oil, Patchouli essential oil, Rosemary essential oil

INDICATIONS AND USAGE

Temporarily protects and helps relieve minor skin irritation due to dryness, eczema, chapped skin, and scaling skin.